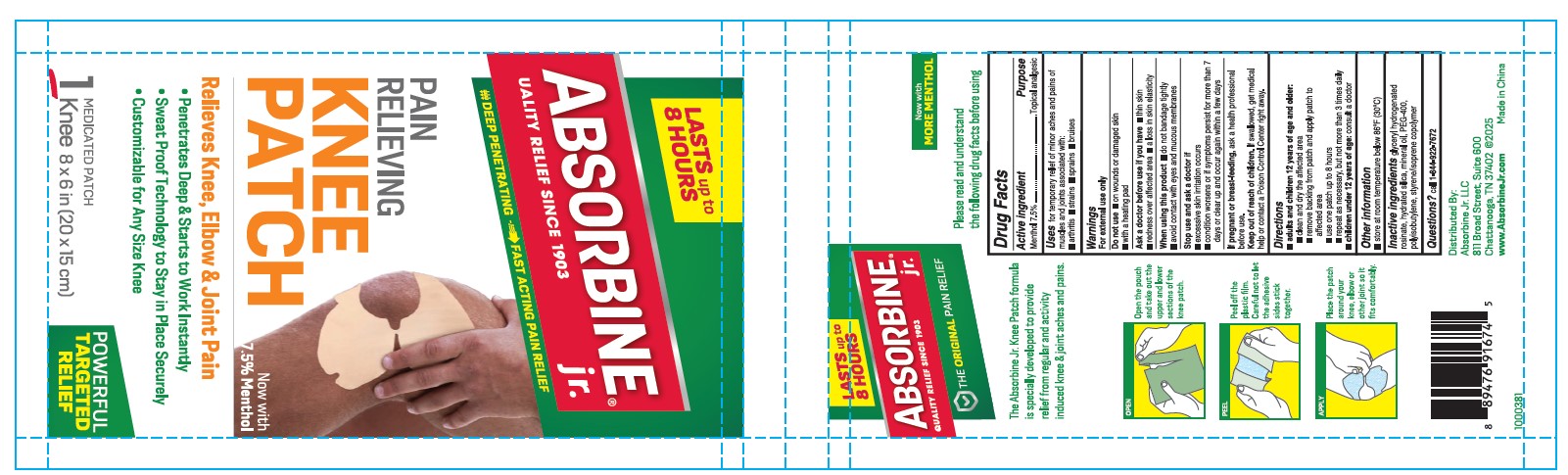 DRUG LABEL: Absorbine Jr. Pain Relieving Knee Patch
NDC: 69693-423 | Form: PATCH
Manufacturer: Clarion Brands, LLC
Category: otc | Type: HUMAN OTC DRUG LABEL
Date: 20251228

ACTIVE INGREDIENTS: MENTHOL 7500 mg/1 h
INACTIVE INGREDIENTS: HYDRATED SILICA; GLYCERYL ROSINATE; STYRENE/ISOPRENE COPOLYMER (28:72; 210000 MW); POLYETHYLENE GLYCOL 400; POLYISOBUTYLENE (1000 MW); MINERAL OIL

ACTIVE INGREDIENT

Menthol 7.5%

PURPOSE

Topical analgesic

INDICATIONS AND USAGE

For temporary relief of minor aches and pains of muscles and joints associated with:

- simple backache
- arthritis
- sprains
- strains
- bruises

WARNINGS

For external use only.

Do not use

- on wounds or damaged skin
- with a heating pad

Ask a doctor before use if you have

- redness over affected area

When using this product

- avoid contact with eyes and mucous membranes
- do not bandage tightly

Stop use and ask a doctor if

- condition worsens or if symptoms persist for more than 7 days or clear up and occur again within a few days
- excessive skin irritation occurs

INDICATIONS AND USAGE

- adults and children 12 years of age and older apply to the affected area no more than 3 to 4 times daily
- open pouch & remove patch
- peel off protective film and apply sticky side to affected area
- children under 12 years of age consult a doctor

INACTIVE INGREDIENT

- glyceryl hydrogenated rosinate
- hydrated silica
- mineral oil
- PEG-400
- polyisobutylene
- styrene/isoprene copolymer

QUESTIONS

call 1-844-822-7672

Keep out of reach of children.

If swallowed, get medical help or contact a Poison Control Center right away.

Ask a doctor before use if you have

- redness over affected area

DOSAGE AND ADMINISTRATION

Menthol 7.5%

PACKAGE LABEL

Lasts up to 8 Hours!
Absorbine jr.®
QUALITY RELIEF SINCE 1903
DEEP PENETRATING & FAST ACTING PAIN RELIEF
PAIN RELIEVING KNEE PATCH

7.5% Menthol
Relieves Knee, Elbow & Joint Pain
• Penetrates Deep & Starts to Work Instantly
• Sweat Proof Technology to Stay in Place Securely
• Customizable for Any Size Knee
Medicated Patch
1 Knee 8 × 6 in (20 × 15 cm)

POWERFUL TARGETED RELIEF

Absorbine jr.®
QUALITY RELIEF SINCE 1903
THE ORIGINAL PAIN RELIEF
The Absorbine Jr. Knee Patch formula is specifically developed

to provide relief from regular and activity induced knee & joint

aches and pains.

Distributed by:
Absorbine Jr. LLC
811 Broad Street, Suite 600
Chattanooga, TN 37402
1000381 @2025
www.absorbinejr.com
Made in China